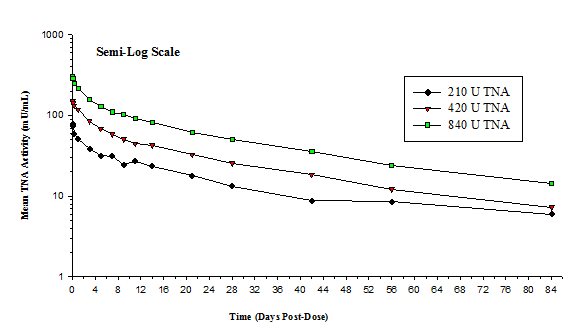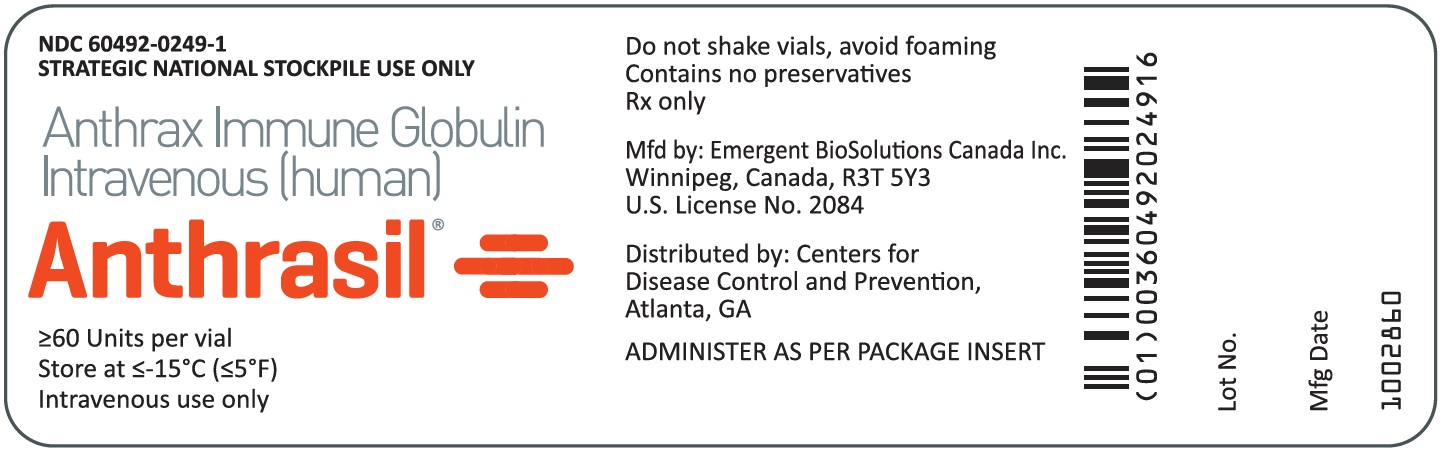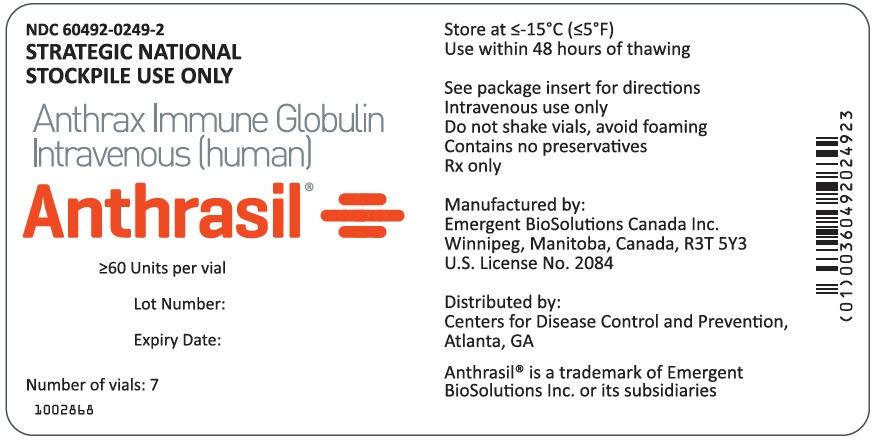 DRUG LABEL: Anthrasil
NDC: 60492-0249 | Form: LIQUID
Manufacturer: Emergent BioSolutions Canada Inc.
Category: other | Type: PLASMA DERIVATIVE
Date: 20251216

ACTIVE INGREDIENTS: ANTHRAX IMMUNE GLOBULIN HUMAN 60 [iU]/35 mL
INACTIVE INGREDIENTS: MALTOSE MONOHYDRATE; POLYSORBATE 80

HIGHLIGHTS OF PRESCRIBING INFORMATION

These highlights do not include all the information needed to use ANTHRASIL™ safely and effectively. See full prescribing information for ANTHRASIL.
ANTHRASIL [Anthrax Immune Globulin Intravenous (Human)], sterile solution for infusion
Initial U.S. Approval: March 24, 2015

WARNING: INTERACTIONS WITH GLUCOSE MONITORING SYSTEMS AND THROMBOSIS

See full prescribing information for complete boxed warning.

- Maltose in immune globulin products, including ANTHRASIL, may give falsely high blood glucose levels with some blood point-of-care glucose testing systems (for example those based on the GDH-PQQ or glucose-dye-oxidoreductase methods) resulting in inappropriate administration of insulin and life-threatening hypoglycemia. To avoid interference by maltose contained in ANTHRASIL, perform blood glucose measurements in patients receiving ANTHRASIL with a glucose-specific method (monitor and test strips).
- Thrombosis may occur with immune globulin products, including ANTHRASIL. Risk factors may include advanced age, prolonged immobilization, hypercoagulable conditions, history of venous or arterial thrombosis, use of estrogens, indwelling vascular catheters, hyperviscosity and cardiovascular risk factors. Thrombosis may occur in the absence of known risk factors.
- For patients at risk of thrombosis, administer ANTHRASIL at the minimum infusion rate practicable. Ensure adequate hydration in patients before administration. Monitor for signs and symptoms of thrombosis and assess blood viscosity in patients at risk of hyperviscosity.

1 INDICATIONS AND USAGE

ANTHRASIL is an Anthrax Immune Globulin Intravenous (Human) indicated for the treatment of inhalational anthrax in adult and pediatric patients in combination with appropriate antibacterial drugs (1).

The effectiveness of ANTHRASIL is based solely on efficacy studies conducted in animal models of inhalational anthrax.

2 DOSAGE AND ADMINISTRATION

For intravenous use only.
Dosing of ANTHRASIL

Patient Group | Dosea | Starting Infusion; Rate (first 30 min) | Incremental Infusion Rate; if Tolerated (every 30 min) | Max Infusion Rate
Adults; (≥17 years) | 7 vials; (420 units) | 0.5 mL/min | 1 mL/min | 2 mL/min
Pediatric; <1 year to ≤16 years | 1–7 vials (60–420 units) based on patient weight | 0.01 mL/kg/min (do not exceed the adult rate) | 0.02 mL/kg/min | 0.04 mL/kg/min (do not exceed the adult rate)
aSelect initial dose based on clinical severity; severe cases may warrant use of 14 vials (840 units) in adults and 2 to 14 vials (based on weight) in pediatric patients weighing >5 kg.

Adjust dose and consider redosing based on clinical severity and response to treatment (2.1)
Weight-based Pediatric Dose

Body Weight (kg) | Vials per Dosea | Body Weight (kg) | Vials per Dose
<5 | 1 | 25 to <35 | 4
<10 | 1 | 35 to <50 | 5
10 to <18 | 2 | 50 to <60 | 6
18 to <25 | 3 | ≥60 | 7
aSelect initial dose based on clinical severity. Dose may be doubled for severe cases in patients >5 kg.

Administer ANTHRASIL by slow intravenous infusion using an infusion pump (maximum 2 mL per minute).

3 DOSAGE FORMS AND STRENGTHS

Each single-use vial contains a minimum potency of ≥60 units by Toxin Neutralization Assay (TNA) (3).

4 CONTRAINDICATIONS

- History of anaphylactic or severe systemic reaction to human immune globulins (4)
- IgA deficiency with antibodies against IgA and a history of IgA hypersensitivity (4)

5 WARNINGS AND PRECAUTIONS

- Hypersensitivity reactions including anaphylaxis (5.1)
- Interference with blood and urine glucose testing (5.2, 5.9)
- Thrombosis may occur. Monitor patients at risk (5.3)
- Monitor renal function and urine output in patients at risk of acute renal dysfunction/failure (5.4)
- Infuse ANTHRASIL at the minimum rate practicable in patients at risk of thrombosis or renal failure (5.5)
- Monitor for clinical signs and symptoms of hemolysis and hemolytic anemia (5.6)
- Aseptic meningitis syndrome (AMS) (5.7)
- Transfusion-related Acute Lung Injury (TRALI) (5.10)
- Transmission of infectious agents from human plasma (5.11)

6 ADVERSE REACTIONS

The most common adverse reactions to ANTHRASIL observed in >5% of healthy volunteers in clinical trials were headache, infusion site pain and swelling, nausea, and back pain (6.1).

To report SUSPECTED ADVERSE REACTIONS, contact Emergent BioSolutions Canada Inc. at 1-800-768-2304 or FDA at 1-800-FDA-1088 or www.fda.gov/medwatch.

8 USE IN SPECIFIC POPULATIONS

- Pregnancy: No human or animal data are available (8.1)

FULL PRESCRIBING INFORMATION

WARNING: INTERACTIONS WITH GLUCOSE MONITORING SYSTEMS AND THROMBOSIS

- Maltose in immune globulin products, including ANTHRASIL, may give falsely high blood glucose levels with some blood point-of-care glucose testing systems (for example those based on the GDH-PQQ or glucose-dye-oxidoreductase methods) resulting in inappropriate administration of insulin and life-threatening hypoglycemia. To avoid interference by maltose contained in ANTHRASIL, perform blood glucose measurements in patients receiving ANTHRASIL with a glucose-specific method (monitor and test strips).
- Thrombosis may occur with immune globulin products, including ANTHRASIL. Risk factors may include advanced age, prolonged immobilization, hypercoagulable conditions, history of venous or arterial thrombosis, use of estrogens, indwelling vascular catheters, hyperviscosity and cardiovascular risk factors. Thrombosis may occur in the absence of known risk factors.
- For patients at risk of thrombosis, administer ANTHRASIL at the minimum infusion rate practicable. Ensure adequate hydration in patients before administration. Monitor for signs and symptoms of thrombosis and assess blood viscosity in patients at risk of hyperviscosity.

1 INDICATIONS AND USAGE

ANTHRASIL is an Anthrax Immune Globulin Intravenous (Human) indicated for the treatment of inhalational anthrax in adult and pediatric patients in combination with appropriate antibacterial drugs.

The effectiveness of ANTHRASIL is based solely on efficacy studies conducted in animal models of inhalational anthrax [See 13.2 Animal Toxicology and/or Pharmacology].

Limitations:

- ANTHRASIL does not have direct antibacterial activity.
- ANTHRASIL does not cross the blood-brain barrier and does not prevent or treat meningitis.
- There have been no studies of ANTHRASIL in the pediatric, geriatric, or obese populations.

2 DOSAGE AND ADMINISTRATION

For intravenous use only.

2.1 Dose

Table 1 ANTHRASIL Dosing Guide and Intravenous Infusion Rate
Patient Group | Dosea | Starting Infusion Rate (first 30 minutes) | Incremental Infusion Rate if Tolerated (every 30 minutes) | Maximum Infusion Rate
Adults; ≥17 years | 7 vials; (420 units) | 0.5 mL/min | 1 mL/min | 2 mL/min
Pediatric; <1 year to ≤16 years | 1–7 vials; (60–420 units) based on patient weight | 0.01 mL/kg/min; (do not exceed the adult rate) | 0.02 mL/kg/min | 0.04 mL/kg/min; (do not exceed the adult rate)
a Select initial dose based on clinical severity; severe cases may warrant use of 14 vials (840 units) in adults and 2 to 14 vials (based on weight) in pediatric patients weighing >5 kg.

Table 2 Pediatric Dosing Guide for ANTHRASILa
Body Weight (kg) | Number of ANTHRASIL Vials per Doseb
<5 | 1
<10 | 1
10 to <18 | 2
18 to <25 | 3
25 to <35 | 4
35 to <50 | 5
50 to <60 | 6
≥60 | 7
a The pediatric dosing is derived from allometric scaling based on observed adult exposure to ANTHRASIL at 420 units by Toxin Neutralization Assay (TNA) dose.
b Select initial dose based on clinical severity. Dose may be doubled for severe cases in patients >5 kg.

The initial dose of ANTHRASIL for the treatment of inhalational anthrax in adults in combination with appropriate antimicrobial therapy is 420 units (seven vials). Data in animal models suggest that administration of higher doses may result in improved survival [See 13.2 Animal Toxicology and/or Pharmacology]. An initial dose of 840 units (14 vials) may be considered, depending on the clinical status of the patient.

Depending on the severity of symptoms and the response to treatment, consider an initial dose of 840 units (14 vials) and repeat dosing especially in patients experiencing substantial hemorrhage as reflected in large transfusion requirements, patients with significant compartmental fluid losses such as from large volume and/or repeated therapeutic thoracentesis and/or abdominal paracentesis, and in patients whose own immune response may be impaired/delayed. Take the magnitude of ongoing blood and fluid losses and the clinical status of the patient into account in determining the time interval between doses when repeat doses are administered. Repeated dosing and single doses greater than 840 units in humans have not been studied. Without substantially delaying therapy, give consideration to performing therapeutic thoracentesis and/or abdominal paracentesis as indicated prior to or concurrently with administration of ANTHRASIL.

2.2 Preparation and Administration

Each vial of ANTHRASIL has a minimum potency of ≥60 units per vial [See 3 DOSAGE FORMS AND STRENGTHS].

1. Bring ANTHRASIL vials to room temperature.
  1. Thaw frozen vials rapidly for immediate use by placing at room temperature for one hour followed by a water bath at 37°C (98.6°F) until thawed.
  2. Alternatively, thaw vials by placing the required number of vials in a refrigerator at 2 to 8°C (36 to 46°F) until the vials are thawed (approximately 14 hours).
  3. Do not thaw in a microwave oven. Do not refreeze vials.
  4. Bring thawed vials to room temperature by letting sit on a bench for a few minutes prior to infusion.
2. Inspect vials to ensure the product is fully thawed and free from discoloration and particulate matter. The solution should be clear or slightly opalescent. Do not use solutions that are cloudy, turbid or have particulates.
3. Inspect vials to ensure there is no damage to the seal or vial. If damaged, do not use and contact the manufacturer.
4. Gently swirl upright vials by hand to ensure uniformity. Do not shake the vial during preparation to avoid foaming.
5. Follow the steps below to prepare the ANTHRASIL infusion bag:
  1. Remove the protective caps from the product vials.
  2. Wipe the exposed central portion of the rubber stopper with an isopropyl alcohol swab.
  3. Withdraw the vial contents of ANTHRASIL into a syringe, aseptically transfer into an appropriately sized intravenous bag and label with the volume to be infused.
  4. No further dilution is required.
  5. Once punctured, use the vial contents to prepare the infusion bag and administer as soon as possible. ANTHRASIL contains no preservative.
6. Administer in an intravenous line with constant infusion pump. Use of an in-line filter is optional.
7. If adverse reactions occur, such as flushing, headache, nausea, changes in pulse rate or blood pressure, slow the rate of infusion or temporarily stop the infusion.

ANTHRASIL vials are for single use only. Discard any unused portion.

3 DOSAGE FORMS AND STRENGTHS

Each vial of ANTHRASIL contains a minimum potency of ≥60 units per vial.

4 CONTRAINDICATIONS

- ANTHRASIL is contraindicated in individuals with a history of anaphylaxis or prior severe systemic reaction associated with the parenteral administration of this or other human immune globulin preparations.
- ANTHRASIL is contraindicated in IgA-deficient patients with antibodies against IgA and a history of IgA hypersensitivity, as it contains trace amounts of IgA (less than or equal to 40 mcg per mL) [See 5.1 Hypersensitivity Reactions].

5 WARNINGS AND PRECAUTIONS

5.1 Hypersensitivity Reactions

Hypersensitivity reactions may occur with ANTHRASIL.

Administer ANTHRASIL in a setting where appropriate equipment, medication (including epinephrine) and personnel trained in the management of hypersensitivity, anaphylaxis and shock are available.

Monitor all patients for signs and symptoms of acute allergic reactions (e.g. urticaria, pruritus, erythema, angioedema, bronchospasm with wheezing or cough, stridor, laryngeal edema, hypotension, tachycardia) during and following the ANTHRASIL infusion. In case of severe hypersensitivity reactions, discontinue the administration of ANTHRASIL immediately and administer appropriate emergency care.

ANTHRASIL contains trace amounts of IgA (less than or equal to 40 mcg per mL). Patients with known antibodies to IgA may have greater risk of developing severe hypersensitivity and anaphylactic reactions. ANTHRASIL is contraindicated in patients with antibodies against IgA and a history of hypersensitivity reaction [See 4 CONTRAINDICATIONS].

5.2 Interference with Blood Glucose Testing

ANTHRASIL contains maltose. Maltose has been shown to give falsely high blood glucose levels in certain types of blood glucose testing systems (for example, by systems based on glucose dehydrogenase pyrroloquinolinequinone (GDH‑PQQ) or glucose‑dye-oxidoreductase methods). Due to the potential for falsely elevated glucose readings (or falsely normal glucose readings when hypoglycemia is present), only use testing systems that are glucose‑specific to test or monitor blood glucose levels in patients receiving ANTHRASIL.

Review the product information of the blood glucose testing system, including that of the test strips, to determine if the system is appropriate for use with maltose-containing parenteral products. If any uncertainty exists, contact the manufacturer of the testing system to determine if the system is appropriate for use with maltose-containing parenteral products.

5.3 Thrombosis

Thrombosis may occur following treatment with immune globulin products, including ANTHRASIL [See BOXED WARNING]. Risk factors include cardiovascular risk factors, advanced age, impaired cardiac output, hypercoagulable disorders, prolonged periods of immobilization, history of arterial or venous thrombosis, estrogen use, indwelling central vascular catheters, and/or known or suspected hyperviscosity. Thrombosis may occur in the absence of known risk factors. Weigh the potential risks and benefits of ANTHRASIL against those of alternative therapies for all patients for whom ANTHRASIL administration is being considered.

Because of the potentially increased risk of thrombosis, consider baseline assessment of blood viscosity in patients at risk for hyperviscosity, including those with cryoglobulins, fasting chylomicronemia/markedly high triacylglycerols (triglycerides), or monoclonal gammopathies.

In patients with risk factors where the benefits of ANTHRASIL administration out-weigh the potential risks of thrombosis, administer ANTHRASIL at the minimum rate of infusion practicable. Ensure adequate hydration in patients before administration. Monitor for signs and symptoms of thrombosis.

5.4 Acute Renal Dysfunction/Failure

Acute renal dysfunction, acute renal failure, osmotic nephropathy, acute tubular necrosis, proximal tubular nephropathy, and death may occur upon use of immune globulin intravenous products, including ANTHRASIL. Use ANTHRASIL with caution in patients with any degree of pre-existing renal insufficiency and in patients at risk of developing renal insufficiency (including, but not limited to those with diabetes mellitus, age greater than 65 years, volume depletion, paraproteinemia, sepsis, and patients receiving known nephrotoxic drugs), administering at the minimum rate of infusion practicable. Ensure that patients are not volume depleted before ANTHRASIL infusion. Do not exceed the recommended infusion rate, and follow the infusion schedule closely. Periodic monitoring of renal function and urine output is important in patients judged to be at increased risk of developing acute renal failure. Assess renal function, including measurement of blood urea nitrogen (BUN) and serum creatinine, before the initial infusion of ANTHRASIL and at appropriate intervals thereafter. If renal function deteriorates, consider discontinuing ANTHRASIL.

Most cases of renal insufficiency following administration of immune globulin products have occurred in patients receiving total doses containing 400 mg per kg of sucrose or greater. ANTHRASIL does not contain sucrose.

5.5 Infusion Rate Precautions

Adverse reactions (such as chills, fever, headache, nausea and vomiting) may be related to the rate of infusion. Follow closely the recommended infusion rate given under 2.1 Dose. Closely monitor and carefully observe patients and their vital signs for any symptoms throughout the infusion period and immediately following an infusion.

5.6 Hemolysis

Hemolytic anemia and hemolysis may develop subsequent to ANTHRASIL administration. ANTHRASIL may contain blood group antibodies that may act as hemolysins and induce in vivo coating of red blood cells with immune globulin, causing a positive direct antiglobulin reaction and hemolysis. Acute hemolysis, including intravascular hemolysis, has been reported following immune globulin administration and delayed hemolytic anemia can develop due to enhanced red blood cell sequestration. Severe hemolysis may lead to renal dysfunction/failure.

The following risk factors may be associated with the development of hemolysis: high doses (e.g., >2 g per kg), given either as a single administration or divided over several days, and non-O blood group (1). Other individual patient factors, such as an underlying inflammatory state (as may be reflected by, for example, elevated C-reactive protein or erythrocyte sedimentation rate), have been hypothesized to increase the risk of hemolysis (2) but their role is uncertain.

Monitor ANTHRASIL recipients for clinical signs and symptoms of hemolysis. Consider appropriate laboratory testing in higher risk patients, including measurement of hemoglobin or hematocrit prior to infusion and within approximately 36 to 96 hours and again approximately seven to 10 days post infusion. If signs and/or symptoms of hemolysis or a significant drop in hemoglobin or hematocrit have been observed after infusion, perform additional confirmatory laboratory testing.

5.7 Aseptic Meningitis Syndrome (AMS)

AMS may occur in association with administration of immune globulin products, including ANTHRASIL. AMS usually is associated with high total doses (>2 g per kg) and begins within several hours to two days following treatment. Discontinuation of treatment has resulted in remission of AMS within several days without sequelae.

AMS is characterized by the following symptoms and signs: severe headache, nuchal rigidity, drowsiness, fever, photophobia, painful eye movements, and nausea and vomiting. Cerebrospinal fluid (CSF) studies are frequently positive with pleocytosis up to several thousand cells per cubic millimeter, predominately from the granulocytic series, and with elevated protein levels up to several hundred mg per dL, but negative culture results. Conduct a detailed neurological examination in patients exhibiting such symptoms and signs, including CSF studies, to rule out other causes of meningitis (particularly anthrax meningitis).

5.8 Monitoring: Laboratory Tests

- Consider periodic monitoring of renal function and urine output in patients judged to be at increased risk of developing acute renal failure. Assess renal function, including measurement of BUN and serum creatinine, before the initial infusion of ANTHRASIL and at appropriate intervals thereafter.
- Because of the potentially increased risk of thrombosis, consider baseline assessment of blood viscosity in patients at risk for hyperviscosity, including those with cryoglobulins, fasting chylomicronemia/markedly high triacylglycerols (triglycerides), or monoclonal gammopathies.
- If signs and/or symptoms of hemolysis are present after an infusion of ANTHRASIL, perform appropriate laboratory testing for confirmation.

If TRALI is suspected, perform appropriate tests for the presence of anti-HLA and anti-neutrophil antibodies in the product. TRALI may be managed using oxygen therapy with adequate ventilatory support.

5.9 Interference with Laboratory Testing

ANTHRASIL contains maltose, which can be misinterpreted as glucose by certain types of blood glucose testing systems (for example, those based on the GDH-PQQ or glucose-dye-oxidoreductase methods). Due to the potential for falsely elevated glucose readings, use only testing systems that are glucose-specific to test or monitor blood glucose levels in patients receiving ANTHRASIL [See BOXED WARNING and 5.2 Interference with Blood Glucose Testing].

Antibodies present in ANTHRASIL may interfere with some serological tests. After administration of immune globulins like ANTHRASIL, a transitory increase of passively transferred antibodies in the patient’s blood may result in positive results in serological testing (e.g. Coombs’ test) [See 5.6 Hemolysis].

Urinalysis after ANTHRASIL administration may result in elevated glucose [See 6.1 Clinical Trials Experience]. As this is a known transient effect, testing should be repeated to determine if further action is warranted.

5.10 Transfusion-related Acute Lung Injury (TRALI)

Noncardiogenic pulmonary edema may occur in patients receiving immune globulin products, including ANTHRASIL. TRALI is characterized by severe respiratory distress, pulmonary edema, hypoxemia, normal left ventricular function, and fever and typically occurs within one to six hours after transfusion.

Monitor recipients for pulmonary adverse reactions. If TRALI is suspected, perform tests for the presence of anti-HLA and anti-neutrophil antibodies in \the product.

5.11 Transmission of Infectious Agents from Human Plasma

Because ANTHRASIL is made from human plasma, it may carry a risk of transmitting blood-borne infectious agents, e.g., viruses, the variant Creutzfeldt-Jakob disease (vCJD) agent, and, theoretically, the Creutzfeld-Jakob disease (CJD) agent. No cases of transmission of viral diseases, vCJD or CJD have been associated with the use of ANTHRASIL.

All infections thought to have been possibly transmitted by this product should be reported by the physician or other health care provider to Emergent BioSolutions Canada Inc. at 1-800-768-2304.

6 ADVERSE REACTIONS

The most common adverse reactions to ANTHRASIL observed in >5% of subjects in the healthy volunteer clinical trial were headache, infusion site pain, nausea, infusion site swelling, and back pain. The safety profile of the product may be different in patients with severe inhalational/systemic anthrax from that seen in the healthy volunteer trial. The incidence and/or severity of some adverse reactions to ANTHRASIL and other intravenous immune globulin products may be related to the total protein/polyclonal antibody load administered.

6.1 Clinical Trials Experience

Because clinical trials are conducted under widely varying conditions, adverse reaction rates observed in the clinical trials of a drug cannot be directly compared to rates in the clinical trials of another drug and may not reflect the rates observed in practice.

In a double blind, randomized, placebo-controlled study designed to assess the safety and pharmacokinetics of three doses of ANTHRASIL after a single intravenous infusion in healthy volunteers, 72 healthy adult subjects were randomized to receive a dose of 210, 420 or 840 units of ANTHRASIL by Toxin Neutralization Assay (TNA) (N=18/dosing group) or an equal volume of saline placebo (N=6/dosing group). A total of 54 healthy volunteers received one of the three ANTHRASIL doses while 18 healthy volunteers received a saline placebo.

A second stage of the study, designed only for additional safety assessment, was a randomized, open-label study in 20 healthy adult volunteers. Subjects were randomized to receive a dose of 840 units by TNA from one of two additional product lots (10 subjects per lot). There was no placebo group.

Table 1 Adverse Reactions Observed in >5% of Subjects Administered ANTHRASIL or Placebo in a Healthy Volunteer Clinical Trial
System Organ Class | Preferred Term | AIGIV Blinded Randomized Group (N=54) |  |  | Placebo (N=18)
System Organ Class | Preferred Term | No. of Events | No. of Subjects | % of Subjects | No. of Events | No. of Subjects | % of Subjects
Gastrointestinal disorders | Nausea | 5 | 5 | 9.3 | 2 | 1 | 5.6
General disorders and administration site conditions | Infusion site pain | 7 | 5 | 9.3 | 0 | 0 | 0.0
General disorders and administration site conditions | Infusion site swelling | 5 | 4 | 7.4 | 0 | 0 | 0.0
Musculoskeletal and connective tissue disorders | Back pain | 2 | 2 | 3.7 | 1 | 1 | 5.6
Nervous system disorders | Headache | 15 | 11 | 20.4 | 3 | 1 | 5.6

There were no serious adverse reactions reported in any of the AIGIV or saline placebo control groups in these studies. Non-serious adverse events and adverse reactions were more frequent in the active AIGIV dosage groups than in the subjects administered placebo.

Headache and back pain rates occurred in a dose-dependent fashion. Back pain was observed with 840 unit doses in five out of 74 subjects (6.8%).

Dose-related elevations in urine glucose also were noted transiently following infusion [See 5.9 Interference with Laboratory Testing].

Infusion of ANTHRASIL was stopped for four subjects due to adverse reactions. One subject was withdrawn due to chest discomfort, flushing, tachycardia and throat tightness.

Patient Experience

Nineteen adult patients with severe systemic anthrax have been dosed with single 420 unit doses of ANTHRASIL and antimicrobial therapy through expanded access use with the Centers for Disease Control and Prevention (CDC): three patients with inhalational anthrax, 15 patients with anthrax due to injection of anthrax-contaminated heroin and one patient with gastrointestinal anthrax.

A total of 16 serious adverse reactions that began within 72 hours of infusion were reported for eight out of 19 patients (42%) as follows: acute respiratory distress syndrome (n=2), pulmonary edema, pleural effusion, acute renal insufficiency/failure (n=4), coagulopathy, cardiac arrest/death (not otherwise specified, n=2), hypotension, ascites, metabolic acidosis, hyperkalemia, and edema/perhipheral edema.

Six deaths were reported including one patient with inhalational anthrax. The cause of death in three of these six expired patients, including the patient who expired with inhalational anthrax, was consistent with progression of anthrax disease or co-morbidities and the cause of death in the remaining three patients was not determined or available.

7 DRUG INTERACTIONS

7.1 Ciprofloxacin and Levofloxacin

Based on animal studies, ANTHRASIL did not interfere with antibiotic therapy. Concomitant administration of ANTHRASIL with levofloxacin or ciprofloxacin in exposed rabbits and cynomolgus macaques, respectively, did not reduce the efficacy of antibacterial therapy.

7.2 Live, Attenuated Vaccines

Immune globulin administration may impair the efficacy of live attenuated vaccines such as measles, rubella, mumps and varicella. Defer vaccination with live virus vaccines until approximately three months after administration of ANTHRASIL. Revaccinate people who received ANTHRASIL shortly after live virus vaccination three months after the administration of the ANTHRASIL.

8 USE IN SPECIFIC POPULATIONS

8.1 Pregnancy

Risk Summary

There are no human data to establish the presence or absence of ANTHRASIL associated risk.

8.2 Lactation

Risk Summary

There are no data to assess the presence or absence of ANTHRASIL in human milk, the effects on the breastfed child or the effects on milk production/excretion.

8.4 Pediatric Use

Safety and effectiveness of ANTHRASIL in the pediatric population (≤16 yrs of age) have not been studied. Allometric scaling was used to derive dosing regimens to provide pediatric patients with exposure comparable to the observed exposure in adults receiving 420 units and 840 units. The dose for pediatric patients is based on body weight.

8.5 Geriatric Use

Safety and effectiveness of ANTHRASIL in the geriatric population (>65 yrs of age) have not been studied.

8.6 Renal Insufficiency

Use ANTHRASIL with caution in patients with any degree of pre-existing renal insufficiency and in patients at risk of developing renal insufficiency (including, but not limited to those with diabetes mellitus, age greater than 65 years, volume depletion, paraproteinemia, sepsis, and patients receiving known nephrotoxic drugs), administering at the minimum rate of infusion practicable. Ensure that patients are not volume depleted before ANTHRASIL infusion. Do not exceed the recommended infusion rate, and follow the infusion schedule closely.

8.7 Use in Obese Population

Safety and effectiveness of ANTHRASIL in the obese population have not been studied.

11 DESCRIPTION

ANTHRASIL, Anthrax Immune Globulin Intravenous (Human), is a sterile solution of purified human immune globulin G (IgG) containing polyclonal antibodies that bind the protective antigen (PA) component of Bacillus anthracis lethal and edema toxins. It is stabilized with 10% maltose and 0.03% polysorbate 80 (pH is between 5.0 and 6.5) and contains no preservative. The product is a clear or slightly opalescent colorless liquid, free of foreign particles, supplied in a 50 mL vial with variable fill volume. The total protein concentration ranges from 40 to 70 mg per mL. An adult dosage of 420 units (seven vials) of ANTHRASIL contains up to 0.368 g protein per kg body weight, and an adult dosage of 840 units (14 vials) contains up to 0.736 g protein per kg body weight. The protein load exposure to pediatric patients due to ANTHRASIL administration may range from 0.32 to 1.26 g per kg of body weight, depending on the weight-based pediatric dose.

ANTHRASIL is prepared using plasma collected from healthy, screened donors who were immunized with BioThrax® (Anthrax Vaccine Adsorbed) to achieve high titers of anti-anthrax antibody (meeting minimum potency specifications) and purified by an anion-exchange column chromatography method. The source plasma is tested by FDA licensed nucleic acid testing (NAT) for human immunodeficiency virus 1 (HIV-1), hepatitis B virus (HBV) and hepatitis C virus (HCV). Plasma also was tested by in-process NAT for hepatitis A virus (HAV) and parvovirus B19 (B19) via minipool testing; the limit for B19 in the manufacturing pool is set not to exceed 10^4 International Units of B19 DNA per mL.

The manufacturing process contains two steps implemented specifically for virus clearance. The solvent and detergent step (using tri-n-butyl phosphate and Triton X-100) is effective in the inactivation of enveloped viruses such as HBV, HCV and HIV. Virus filtration, using a Planova 20N virus filter, is effective for the removal of viruses based on their size, including some non-enveloped viruses. These two viral clearance steps are designed to increase product safety by reducing the risk of transmission of enveloped and non-enveloped viruses. In addition to these two specific steps, the process step of anion-exchange chromatography was identified as contributing to the overall viral clearance capacity for small non-lipid enveloped viruses.

The inactivation and reduction of known enveloped and non-enveloped model viruses were validated in laboratory studies as summarized in Table 2. The viruses employed for spiking studies were selected to represent those viruses that are potential contaminants in the product, and to represent a wide range of physiochemical properties in order to challenge the manufacturing process’s ability for viral clearance in general.

Table 2 Virus Reduction Values (Log10) Obtained through Validation Studies
Enveloped | Enveloped |  |  | Non-Enveloped
Genome | RNA |  | DNA | RNA |  | DNA
Virus | HIV-1 | BVDV | PRV | HAV | EMC | MMV | PPV
Family | Retrovirus | Flavivirus | Herpes virus | Picornavirus |  | Parvovirus
Size (nm) | 80–100 | 50–70 | 120–200 | 25–30 | 30 | 20–25 | 18–24
Anion Exchange Chromatography (partitioning) | Not evaluated |  |  | 2.3 | n.e. | 3.4 | n.e.
20N Filtration (size exclusion) | ≥4.7 | ≥3.5 | ≥5.6 | n.e. | 4.8 | n.e. | 4.1
Solvent/Detergent (inactivation) | ≥4.7 | ≥7.3 | ≥5.5 | Not evaluated
Total Reduction (log10) | ≥9.4 | ≥10.8 | ≥11.1 | 2.3 | 4.8 | 3.4 | 4.1
Abbreviations:
BVDV = Bovine viral diarrhea virus; model virus for hepatitis C virus (HCV) and West Nile virus (WNV)
DNA = Deoxyribonucleic Acid
EMC = Encephalomyocarditis virus; model for HAV and for small non-enveloped viruses in general
HIV-1 = Human immunodeficiency virus-1; relevant virus for HIV-1 and model for HIV-2
HAV = Human hepatitis A virus; relevant virus for HAV and model for small non-enveloped viruses in general
MMV = Murine minute virus; model for human B19 parvovirus and for small non-enveloped viruses in general
n.e. = Not evaluated
PPV = Porcine parvovirus; model for human B19 parvovirus and for small non-enveloped viruses in general
PRV = Pseudorabies virus; model for large enveloped DNA viruses, including herpes
RNA = Ribonucleic Acid

The product potency, as determined by an in vitro toxin neutralization assay (TNA), is expressed in arbitrary units by comparison to a standard calibrated against the Centers for Disease Control and Prevention (CDC) Reference Serum standard. Each vial contains approximately 40 to 70 mg per mL total protein and ≥60 units of toxin neutralizing activity. The product contains ≤40 mcg per mL of immune globulin A (IgA) as well as residual amounts of solvent and detergent, which are used to inactivate lipid-enveloped viruses.

12 CLINICAL PHARMACOLOGY

12.1 Mechanism of Action

The polyclonal immune globulin G in ANTHRASIL is a passive immunizing agent that neutralizes anthrax toxin. ANTHRASIL binds to protective antigen (PA) to prevent PA mediated cellular entry of anthrax edema factor and lethal factor. ANTHRASIL is administered in combination with appropriate antibiotic therapy as the product by itself is not known to have direct antibacterial activity against anthrax bacteria, which otherwise may continue to grow and produce anthrax toxins.

12.3 Pharmacokinetics

The mean TNA activities for three doses of ANTHRASIL (210, 420 and 840 units TNA) in the clinical trial in healthy volunteers [See 14 CLINICAL STUDIES] are plotted on a semi-log scale in Figure 1. The pharmacokinetics of ANTHRASIL after intravenous infusion of the three dose levels were characterized; the peak levels of ANTHRASIL were reached immediately after infusion and then declined over the duration of study (84 days). The mean TNA activity remained above the lower limit of quantitation (5 milliunits per mL) over the entire 84-day post-dose period for the three doses studied.

Figure 1 Mean TNA Activities for Three Doses of ANTHRASIL

A summary of the mean pharmacokinetic results for the TNA data collected in the healthy volunteer study is presented in Table 3.

Table 3 Summary of Mean PK Results by Treatment (TNA Data)
PK Parameters | Dose Levels
PK Parameters | 210 U TNA | N | 420 U TNA | N | 840 U TNA | N
Arithmetic Mean (CV%)
AUC0-t (mU·d/mL) | 1031.8 (23.3) | 15 | 2176.7 (18.9) | 17 | 4271.0 (22.3) | 16
AUC0-∞ (mU·d/mL) | 1277.5 (27.7) | 7 | 2536.7 (14.7) | 16 | 4788.8 (26.5) | 15
Cmax (mU/mL) | 83.0 (13.4) | 15 | 156.4 (21.7) | 17 | 316.7 (18.3) | 16
t½ (d) | 24.3 (33.3) | 7 | 28.3 (19.9) | 16 | 28.0 (25.2) | 15
CL (mL/d) | 174.2 (24.1) | 7 | 169.7 (17.9) | 16 | 188.6 (29.5) | 15
Vd (mL) | 5714.8 (11.4) | 7 | 6837.2 (20.4) | 16 | 7238.2 (19.4) | 15
Median (Min-Max)
Tmax (d) | 0.116 | 15 | 0.120 | 17 | 0.169 | 16
Tmax (d) | (0.109–1.068) |  | (0.120–0.412) |  | (0.165–0.459)

In comparison to healthy subjects, patients with inhalational anthrax are expected to initially have greater clearance of anti-PA antibodies and lower AUC from ANTHRASIL administration due to the presence of PA antigen.

Mean PK results (TNA data) were evaluated by sex and revealed no sex-related differences over the dose range studied. Systemic exposure of ANTHRASIL increased in a dose-proportional manner over the dose range studied. ANTHRASIL has a serum elimination half-life of 24 to 28 days in healthy humans.

Inhalational anthrax patients, concomitantly treated with antibiotics and a single 420 unit TNA dose of ANTHRASIL, exhibited increases in serum and pleural anti-PA levels; these levels remained at >50% of the peak anti-PA levels over the next five days. The peak serum anti-PA levels in these patients following ANTHRASIL administration (132 to 160 mcg/mL, mean 145 mcg/mL) overlapped with those obtained with the 420 unit dose in healthy volunteers (135 to 250 mcg/mL, mean 190 mcg/mL, median 192 mcg/mL), although mean levels were approximately 25% lower in the inhalational anthrax patients. In the three inhalational anthrax patients, serum and pleural levels of lethal factor declined after initiation of antibiotics and further decreased over the period of five days following ANTHRASIL administration; however, due at least in part to ANTHRASIL targeting the PA component of lethal toxin, plasma and pleural fluid lethal factor levels remained detectable when measured two to five days following ANTHRASIL administration.

Because the effectiveness of ANTHRASIL cannot ethically be tested in placebo-controlled trials in humans, a comparison of ANTHRASIL exposures achieved in healthy human subjects to those observed in animal models of inhalational anthrax in therapeutic efficacy studies was necessary to support the dosage regimen. A dose of 420 units has a similar exposure to the efficacious dose of 15 U/kg administered to New Zealand white rabbits and cynomolgus macaques. In cynomolgus macaques treated with ANTHRASIL monotherapy, a higher dose of 30 U/kg, with a similar exposure to a human dose of 840 units, may result in improved survival [See 13.2 Animal Toxicology and/or Pharmacology]. As a result, the initial dosing regimen is given as a range of 420 to 840 units, and the recommended regimen includes the potential for repeat dosing.

13 NONCLINICAL TOXICOLOGY

Immune globulins are normal constituents of the human body. Toxicology studies have not been performed with ANTHRASIL or its components.

The evaluation of new treatment options for anthrax using placebo-controlled human trials is unethical and infeasible. Therefore, the effectiveness of ANTHRASIL for treatment of inhalational anthrax is based on well controlled efficacy studies conducted in rabbits and cynomolgus macaques.

13.2 Animal Toxicology and/or Pharmacology

Anthrax infected New Zealand white rabbits and cynomolgus macaques administered an intravenous injection of ANTHRASIL (15 units TNA per kg) that did not survive their infection showed an increase in the severity and/or incidence of central nervous system lesions (bacteria, hemorrhage and necrosis) as compared to intravenous immune globulin (“placebo”) treated animals who also did not survive the infection. The mean time to death between non-surviving ANTHRASIL and placebo treated animals was comparable.

Surviving rabbits had no evidence of central nervous system lesions at the end of the study. No surviving cynomolgus macaques in monotherapeutic studies were tested for central nervous system lesions.

Monotherapeutic Studies in Animal Models

In a monotherapeutic efficacy study, rabbits were exposed to a target dose of 200 x LD50 aerosolized anthrax spores and then administered 15 units per kg of ANTHRASIL at the onset of toxemia, as determined by the presence of PA in serum samples. Detection of PA was used as the trigger for initiation of treatment, while bacteremia status provided a retrospective confirmation of disease. Ninety-eight (98) percent of the treated animals were bacteremic prior to treatment. Of the animals that were toxemic and bacteremic prior to treatment, ANTHRASIL treatment resulted in a 26% survival in comparison to a 2% survival with IGIV placebo treatment (Table 4) over the 36 day duration of the study. ANTHRASIL treatment resulted in a significant decrease in the proportion of rabbits that were toxemic or bacteremic. The time to resolution of toxemia (p=0.0006) or bacteremia (p=0.0074) was also significantly reduced in rabbits that received ANTHRASIL.

Efficacy of ANTHRASIL was also assessed in cynomolgus macaques exposed to a target dose of 200 x LD50 aerosolized anthrax spores. Treatment with placebo or one of three dose levels of ANTHRASIL was initiated after animals became toxemic (positive for PA detection in serum samples), and bacteremia status provided a retrospective confirmation of disease. Survival was assessed over a period of 88 days in toxemic animals that were confirmed to be bacteremic at the time of treatment. Survival was 0% in placebo treated animals. Animals treated with 7.5 units per kg exhibited 36% survival, those treated with 15 units per kg exhibited 43% survival, and those treated with 30 units per kg exhibited 70% survival (Table 4). Compared to placebo, these survival rates were statistically significant at p=0.0451, 0.0339, and 0.0031, respectively The differences in survival between the 7.5, 15, and 30 unit per kg doses of ANTHRASIL were not statistically significant. ANTHRASIL treated animals showed a statistically significant reduction in anthrax toxin when compared to placebo treated animals.

Table 4 Survival Rates in NZW Rabbits and Cynomolgus Macaques Treated with ANTHRASIL
 | NZW Rabbits at 36 Days PI |  | Cynomolgus Macaques at 28 Days PI
 | No. Survivors (%)a | p-Valueb | No. Survivors (%)a | p-Valuec
Placebo | 1/48 (2) | – | 0/11 (0) | –
ANTHRASIL 7.5 U/kgd | – | – | 4/11 (36) | 0.0451
ANTHRASIL 15 U/kg | 13/50 (26) | 0.0009 | 6/14 (43) | 0.0339
ANTHRASIL 30 U/kgd | – | – | 7/10 (70) | 0.0031
a Survival among animals that were bacteremic and toxemic prior to treatment
b Two-sided Fisher’s exact test
c Bonferroni-Holm adjusted one-sided Fisher’s exact test
d Dose not evaluated in rabbits in this study
PI = Post-infection

ANTHRASIL Efficacy in Combination with Antibiotics

The efficacy of ANTHRASIL administered with levofloxacin was determined in New Zealand white rabbits with systemic disease. No significant difference between the control (normal immune globulin [IGIV] plus levofloxacin) and treatment groups (ANTHRASIL plus levofloxacin) was seen when combination treatment was delayed up to 60 hours post-challenge. There was no observed antagonism between levofloxacin and ANTHRASIL in this study. This study also supported that ANTHRASIL effectively cleared toxemia when administered with antibiotics. In ANTHRASIL treated groups, all animals cleared PA toxemia post-ANTHRASIL administration and only 4/31 (13%) of ANTHRASIL treated animals exhibited a single transient positive PA result for toxemia at the 12 or 18 hour time point post-dosing. Placebo control animals exhibited more persistent toxemia, with 26/32 (81%) having positive PA results for 18 to 90 hours post-treatment.

In a second study, treatment was delayed beyond 60 hours to simulate a clinical scenario. When combination treatment was initiated at 60, 72, 84 or 96 hours post anthrax exposure, differences in survival were seen, but no statistically significant added survival benefit was observed between groups that received placebo (IGIV plus levofloxacin) or ANTHRASIL (15 units per kg plus levofloxacin). An increase in survival was observed with ANTHRASIL when treatment was delayed to 96 hours post exposure, but was not statistically significant. When treatment was delayed to 96 hours, survival was 25% (2/8) in the antibiotic plus IGIV control group and 71% (5/7) in the ANTHRASIL plus levofloxacin group. A marginal improvement of 10 to 15% was observed at other time points, suggesting a trend in added benefit with ANTHRASIL. This study also demonstrated a significant effect of ANTHRASIL on toxemia. The majority of ANTHRASIL treated animals became negative for PA (toxemia) within one hour post-infusion of ANTHRASIL and remained negative, even with the delayed treatment from 60 to 96 hours post-anthrax challenge and high levels of toxemia pretreatment. In contrast, placebo treated animals remained toxemic up to three days after initiating antibiotic treatment.

The efficacy of ANTHRASIL co-administered with levofloxacin was evaluated in New Zealand white rabbits when treatment was delayed to 96 hours after anthrax spore inhalation. The dose of levofloxacin was chosen to yield a comparable exposure to that achieved by the recommended dose in humans. Of the animals that survived to be treated (19% of those challenged), antibacterial drug plus ANTHRASIL (15 units per kg) resulted in 58% (18/31) survival compared to 39% (13/33) survival in rabbits treated with antibacterial drug and IGIV placebo (p=0.14, Z-test).

When animals were stratified by pre-treatment toxemia (PA) in a post hoc analysis, added benefit was observed in animals treated with ANTHRASIL and levofloxacin when they had pre-treatment PA levels between 200 and 800 ng/mL (p=0.02, Fisher’s exact test). When pre-treatment toxemia was low (PA <200 ng/mL), survival was greater than 90% in all animals, regardless of treatment (Table 5). Animals with very high levels of toxemia (>800 ng/mL) did not survive irrespective of the treatment administered.

Table 5 Survival Rates in New Zealand White Rabbits Stratified by Pre-treatment PA Levels
Pre-treatment PA (ng/mL) | IGIV Placebo + Levofloxacin (%) | ANTHRASIL + Levofloxacin (%)
<200 | 11/12 (91.7) | 8/9 (88.9)
200–800 | 2/11 (18.2) | 10/14 (71.4)
>800 | 0/10 (0) | 0/8 (0)
All pre-treatment PA levels | 13/33 (39.4) | 18/31 (58.1)

ANTHRASIL and antibiotic combination treatment was also studied in the cynomolgus macaque model of inhalational anthrax. In this study, delay of initiation of treatment to 64 hours post anthrax exposure resulted in 75% (9/12) survival in the placebo plus ciprofloxacin treatment group versus 83% (10/12) survival in the ANTHRASIL (15 units per kg) plus ciprofloxacin group (p=1).

No antagonism of ANTHRASIL when administered with antibiotic as a concomitant therapy was observed.

ANTHRASIL in Post-exposure Prophylaxis

A post exposure prophylactic study assessed the survival following aerosol exposure to a lethal dose of anthrax spores (200 x LD50) in New Zealand white rabbits administered ANTHRASIL (7.5, 15 or 30 units TNA per kg) at 30 hours post-anthrax challenge compared to placebo controls. All three doses of ANTHRASIL improved survival when given 30 hours post-anthrax challenge. When animals that were both bacteremic and toxemic were treated at 30 hours following challenge, there was a 22% (2/9) survival with a dose of 15 units TNA per kg and a 33% (4/12) survival with a dose of 30 units TNA per kg. All rabbits in the placebo arm died.

14 CLINICAL STUDIES

Because it is not ethical or feasible to conduct placebo-controlled clinical trials in humans with inhalational anthrax, the effectiveness of ANTHRASIL is based on efficacy studies demonstrating a survival benefit in animal models of inhalational anthrax infection [See 13.2 Animal Toxicology and/or Pharmacology]. The safety has been assessed in healthy adults and in a limited number of patients with anthrax who were treated with ANTHRASIL under expanded access use.

Safety and Pharmacokinetics of ANTHRASIL in Healthy Volunteers

In a double blind, randomized, placebo-controlled study designed to assess the safety and pharmacokinetics of three doses of ANTHRASIL after a single intravenous infusion in healthy volunteers, a total of 72 healthy adult subjects were randomized to receive a dose of 210, 420 or 840 units of ANTHRASIL by TNA (N=18/dosing group) or an equal volume of saline placebo (N=6/dosing group).

A second stage of this study, designed only for additional safety assessment, was a randomized, open-label study in 20 healthy adult volunteers. Subjects were randomized to receive a dose of 840 units by TNA from one of two additional product lots (10 subjects per lot). There was no placebo group [See 6 ADVERSE REACTIONS and 12.3 Pharmacokinetics].

Patient Experience

Nineteen adult patients have been treated with ANTHRASIL under expanded access use, including three patients with inhalational anthrax, one patient with gastrointestinal anthrax and 15 patients with injectional anthrax due to injection of anthrax-contaminated heroin. Patients were receiving antimicrobial therapy before, during and after ANTHRASIL administration.

In patients with inhalational anthrax, two out of three patients treated with ANTHRASIL plus antimicrobial therapy survived and one died from progression of anthrax disease, systemic candidiasis and multiorgan failure. Among the 15 patients with injectional anthrax treated with ANTHRASIL plus antibiotics, 10 survived and five died (two from progression of anthrax disease; the cause of death was not determined or available for three patients). The single patient with gastrointestinal anthrax treated with ANTHRASIL survived. Therapy for these systemic anthrax cases included aggressive supportive measures including mechanical ventilation and pulmonary/abdominal fluid drainage.

In the three inhalational patients, the ANTHRASIL dose of 420 units by TNA resulted in increased anti-PA levels (correlating with increased TNA activity); these levels remained stable up to seven to 20 days post-administration, probably reflecting the rising antibody production by the patient at the same time that the exogenously-administered antibody was being cleared.

In some injectional anthrax cases, complicated by hemorrhage and pleural and/or peritoneal fluid losses from thoracentesis and/or paracentesis, serum anti-PA antibody levels fell as much as approximately 90% from their post-ANTHRASIL peak levels by 24 hours following ANTHRASIL administration. In the gastrointestinal anthrax patient, serum anti-PA levels were observed prior to ANTHRASIL infusion with further increases in anti-PA levels post-administration and maintenance of anti-PA above pre-administration levels for 11 days was observed.

15 REFERENCES

1. Kahwaji J, Barker E, Pepkowitz S, Klapper E, Villicana R, Peng A, et al. Acute hemolysis after high-dose intravenous immunoglobulin therapy in highly HLA sensitized patients. Clin J Am Soc Nephrol. 2009 December;4;1993–97.
2. Daw Z, Padmore R, Neurath D, Cober N, Tokessy M, Desjardins D, et al. Hemolytic transfusion reactions after administration of intravenous immune (gamma) globulin: a case series analysis. Transfusion. 2008;48(8):1598-601.

16 HOW SUPPLIED/STORAGE AND HANDLING

16.1 How Supplied

NDC 60492-0249-1 for single vial

NDC 60492-0249-2 for shelf carton containing seven vials

ANTHRASIL is supplied as a 50 mL single dose vial fitted with a rubber stopper and a plastic cap. Each vial, regardless of fill volume, contains ≥60 units. It is packaged in a shelf carton with seven vials and a package insert.

ANTHRASIL does not contain natural rubber latex.

16.2 Storage and Handling

Store frozen at or below ≤-15°C (≤5°F) until required for use. Do not use after expiration date.

Once punctured, use the vial contents to prepare the infusion bag and infuse as soon as possible. ANTHRASIL contains no preservative.

Do not refreeze, reuse or save ANTHRASIL for future use.

Discard any partially used vials.

17 PATIENT COUNSELING INFORMATION

See FDA-approved patient labeling (Patient Information).

Discuss the risks and benefits of this product with the patient or their legally authorized representative before administering it to the patient.

- Inform patients of the potential for hypersensitivity reactions, especially in individuals with previous reactions to human immune globulin and in individuals deficient in IgA. Advise patients to be aware of the following symptoms associated with allergic reactions: hives, rash, chest tightness, wheezing, shortness of breath, or feeling light headed or dizzy when they stand. Patients should be cautioned to seek medical attention immediately should they experience any one or more of the above mentioned symptoms, as well as other side effects including injection site pain, chills, fever, headache, nausea, vomiting, and joint pain.
- Advise patients that the maltose contained in ANTHRASIL can interfere with some types of blood glucose monitoring systems. Advise patients to use only testing systems that are glucose‑specific for monitoring blood glucose levels as the interference of maltose could result in falsely elevated glucose readings that could lead to untreated hypoglycemia or to inappropriate insulin administration, resulting in life-threatening hypoglycemia.
- Inform patients that ANTHRASIL is an immune globulin product; therefore, there is the potential risk of developing other reactions observed with the immunoglobulin product class such as thrombosis, hemolysis, aseptic meningitis syndrome (AMS), transfusion-related acute lung injury (TRALI), acute respiratory distress syndrome (ARDS) and acute renal dysfunction or failure.
- Advise patients that ANTHRASIL may impair the effectiveness of certain live virus vaccines such as measles, rubella (i.e. German measles), mumps, and varicella (i.e. chickenpox).
- Inform patients that ANTHRASIL is prepared from human plasma. Products made from human plasma may contain infectious agents such as viruses that can cause disease.
- Inform patients that the efficacy of ANTHRASIL is based solely on efficacy studies demonstrating a survival benefit in animals and that the effectiveness of ANTHRASIL has not been tested in humans with anthrax. The safety of ANTHRASIL has been tested in healthy adults.

Manufactured by:

Emergent BioSolutions Canada Inc.
155 Innovation Drive
Winnipeg, MB Canada
R3T 5Y3

US License No. 2084

PATIENT INFORMATION

ANTHRASIL [Anthrax Immune Globulin Intravenous (Human)]

What is anthrax?

Anthrax is a serious disease caused by a germ called Bacillus anthracis. This germ makes a poison called a toxin. People who are exposed to anthrax germs are at risk of serious illness, including death. You/your child cannot get anthrax from another person. Symptoms of anthrax disease usually start within seven days of breathing in anthrax germs, but can take up to six or seven weeks to appear.

- Early symptoms can be any of the following: fever, chills, tiredness, cough, muscle aches and headache.
- Later symptoms can be any of the following: shortness of breath, chest discomfort, confusion or nausea.

What is ANTHRASIL?

Medicines like antibiotics can kill anthrax germs. However, the anthrax poison (toxin) may continue to cause severe sickness even after the germs are gone. When someone gets the anthrax vaccine, their body’s immune system makes antibodies against anthrax. Antibodies help to fight off disease and can also help to fight off the anthrax poison.

ANTHRASIL [Anthrax Immune Globulin Intravenous (Human)] is made by taking anthrax antibodies from well people who have been vaccinated. It does not contain the anthrax germ or poison. The antibodies in ANTHRASIL can then be given to someone with anthrax. This may make the sick person’s disease less severe, decrease the duration of illness and increase their chance of surviving.

The effectiveness of ANTHRASIL has been studied only in animals.

The safety of ANTHRASIL was studied in healthy adults. There have been no studies of ANTHRASIL in persons less than 17 years of age.

Who should use ANTHRASIL?

Your doctor may give you ANTHRASIL if they suspect that you/your child have been exposed to anthrax and may have anthrax in your lungs.

You should get the treatment as quickly as possible to stop the progression of the illness.

Before you receive ANTHRASIL, tell your healthcare provider about all of your medical conditions, including if you are:

- Allergic to any of the ingredients in ANTHRASIL
- Deficient for immune globulin A (IgA)
- Pregnant or planning to become pregnant. It is not known if ANTHRASIL will harm your unborn baby.
- Breastfeeding or plan to breastfeed. It is not known if ANTHRASIL passes into your breast milk. You and your healthcare provider should decide if you will receive ANTHRASIL or breastfeed.
- Diabetic. ANTHRASIL contains maltose, which can give false readings on some glucose testing meters. If you are diabetic, ask your doctor what types of glucose testing meters can be used safely while you are getting ANTHRASIL.

Tell your healthcare provider about all the medicines you take, including prescription and non-prescription medicines, vitamins and herbal supplements.

How will you receive ANTHRASIL?

ANTHRASIL is given as an infusion into your vein. Your doctor will determine the dose of ANTHRASIL. The treatment may take several hours to administer. Your doctor will decide if you need more than one infusion.

What are the possible side effects of ANTHRASIL?

The most common side effects of ANTHRASIL are:

- Headache
- Pain at site of needle entry
- Nausea
- Swelling at site of needle entry
- Back pain

ANTHRASIL can cause allergic reactions. Tell your doctor right away if you have trouble breathing, swelling of your tongue or lips, a very fast heart rate, or feel very weak because these symptoms can be signs of a serious allergic reaction.

Talk to your doctor about any side effects that concern you. You can ask your doctor for additional prescribing information that is available to healthcare professionals.

What other information do you need to know about ANTHRASIL?

ANTHRASIL is made from human plasma. The plasma donors are carefully screened and the plasma is carefully cleaned, but there is a small risk that it may give you a virus. Talk to your doctor if you have any symptoms that concern you.

Tell your doctor if you have recently received a vaccine of any sort, or plan to be vaccinated. Use of ANTHRASIL may cause vaccines such as measles, rubella, mumps and varicella to not work as well. Vaccination with some vaccines may need to be delayed until approximately three months after use of ANTHRASIL. If you received ANTHRASIL shortly after a vaccination you may need to be re-vaccinated three months after the administration of ANTHRASIL. Talk to your doctor.

You may report side effects directly to Emergent BioSolutions Canada Inc. at 1-800-768-2304 or to the FDA’s MedWatch reporting system at 1-800-FDA-1088.

Manufactured by:

Emergent BioSolutions Canada Inc.
155 Innovation Drive
Winnipeg, MB Canada
R3T 5Y3

US License No. 2084